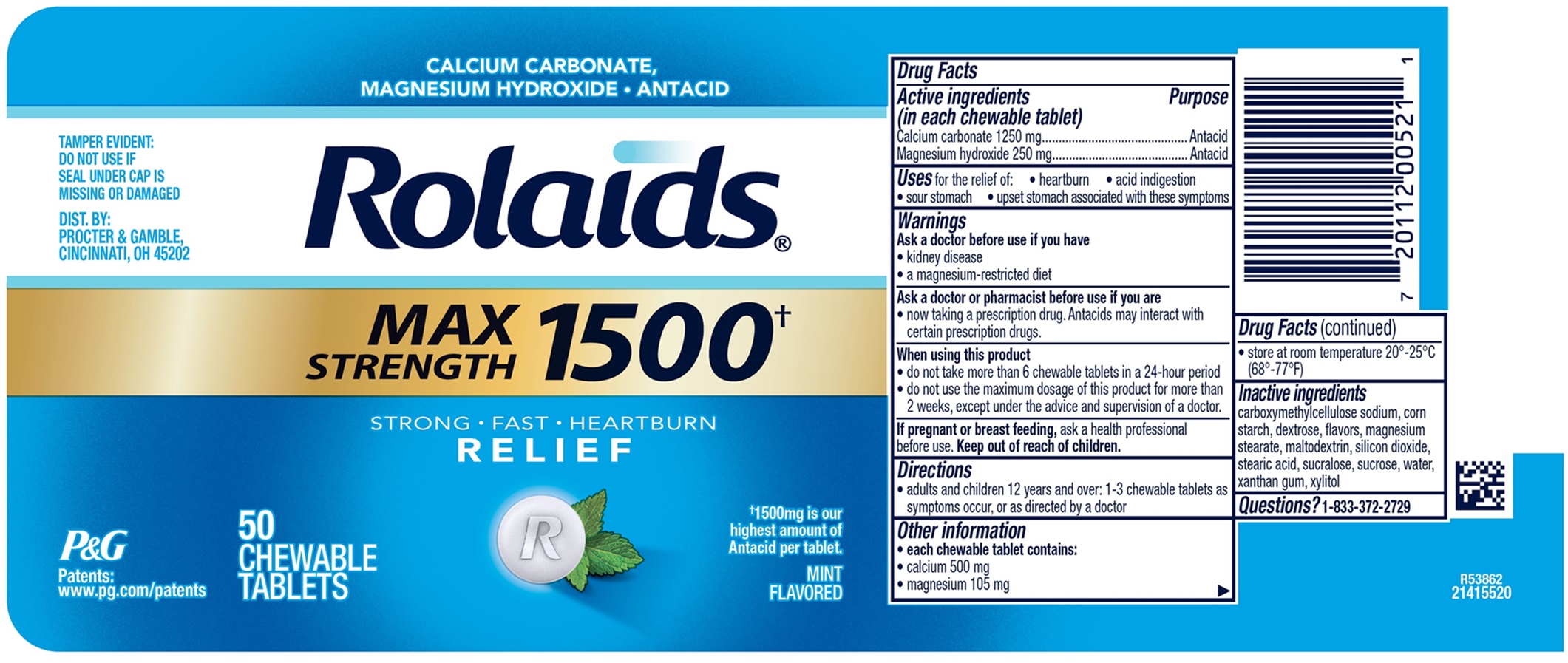 DRUG LABEL: Rolaids
NDC: 84126-373 | Form: TABLET, CHEWABLE
Manufacturer: THE PROCTER & GAMBLE MANUFACTURING COMPANY
Category: otc | Type: HUMAN OTC DRUG LABEL
Date: 20260109

ACTIVE INGREDIENTS: CALCIUM CARBONATE 1250 mg/1 1; MAGNESIUM HYDROXIDE 250 mg/1 1
INACTIVE INGREDIENTS: DEXTROSE; MAGNESIUM STEARATE; SILICON DIOXIDE; STEARIC ACID; SUCRALOSE; SUCROSE; MALTODEXTRIN; CARBOXYMETHYLCELLULOSE SODIUM; STARCH, CORN; WATER; XANTHAN GUM; XYLITOL

Rolaids MAX STRENGTH 1500†, Chewable Tablets

Rolaids MAX STRENGTH 1500†, Chewable Tablets

Drug Facts

Active ingredients

(in each chewable tablet)
Calcium carbonate 1250 mg
Magnesium hydroxide 250 mg

Purpose

Antacid

Antacid

Uses

for the relief of:

- heartburn
- acid indigestion
- sour stomach
- upset stomach associated with these symptoms

Warnings

Ask a doctor before use if you

- kidney disease
- a magnesium-restricted diet

Ask a doctor or pharmacist before use if you

- now taking a prescription drug. Antacids may interact with certain prescription drugs.

When using this product

- do not take more than 6 chewable tablets in a 24-hour period
- do not use the maximum dosage of this product for more than 2 weeks, except under the advice and supervision of a doctor.

If pregnant or breast feeding,

ask a health professional before use.

Directions

- adults and children 12 years and over: 1-3 chewable tablets as symptoms occur, or as directed by a doctor.

Other information

- each chewable tablet contains:
- calcium 500 mg
- magnesium 105 mg
- store at room temperature 20° - 25°C (68° - 77°F)

Inactive ingredients

carboxymethylcellulose sodium, corn starch, dextrose, flavors, magnesium stearate, maltodextrin, silicon dioxide, stearic acid, sucralose, sucrose, water, xanthan gum, xylitol

Questions?

1-833-372-2729

TAMPER EVIDENT: DO NOT USE IF SEAL UNDER CAP IS MISSING OR DAMAGED

DIST. BY: PROCTER & GAMBLE, CINCINNATI, OH 45202

PRINCIPAL DISPLAY PANEL

CALCIUM CARBONATE,

MAGNESIUM HYDROXIDE · ANTACID

Rolaids

MAX STRENGTH 1500†

STRONG · FAST · HEARTBURN

RELIEF

†1500mg is our highest amount of Antacid per tablet.

MINT FLAVORED

50 CHEWABLE TABLETS